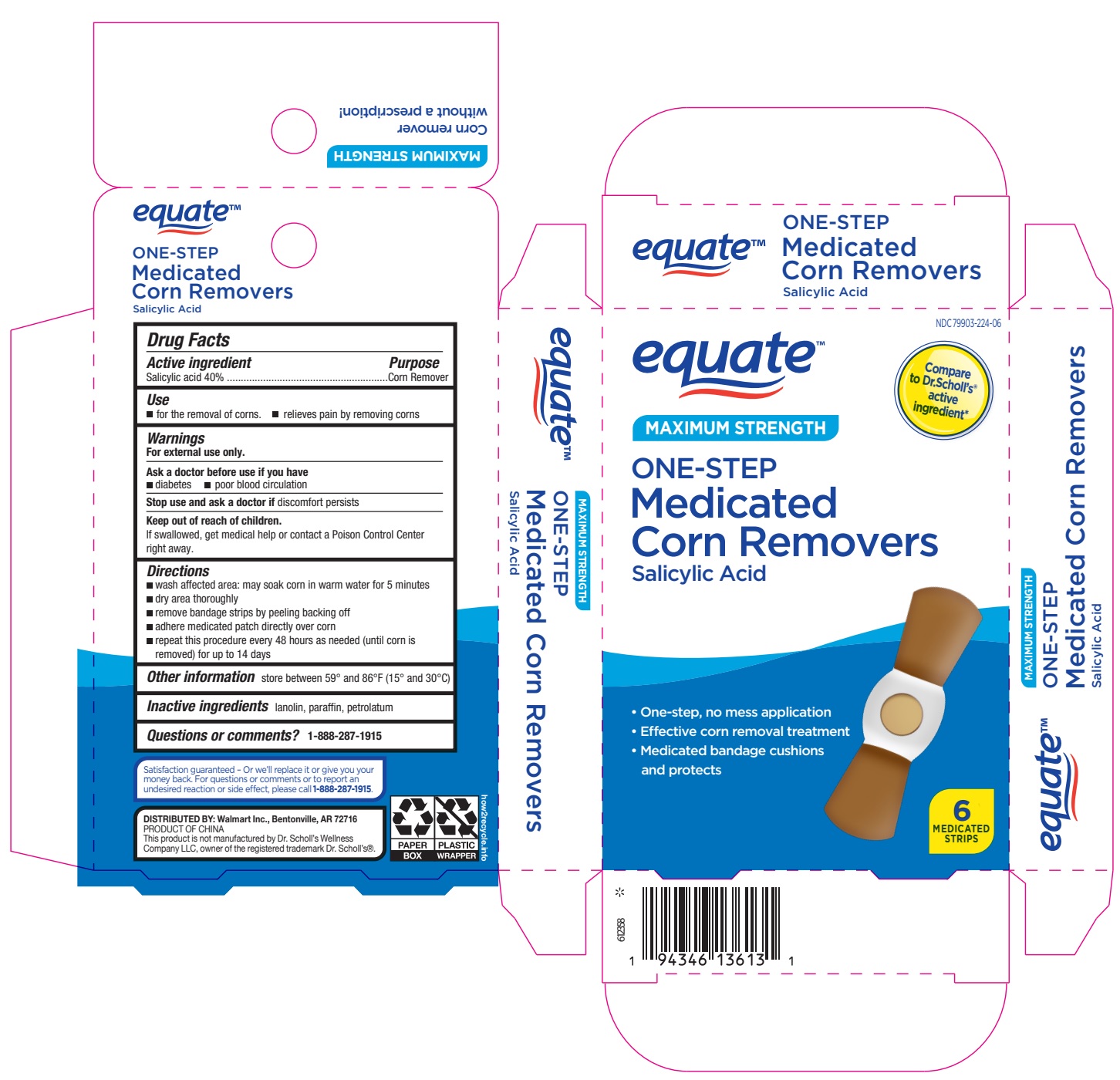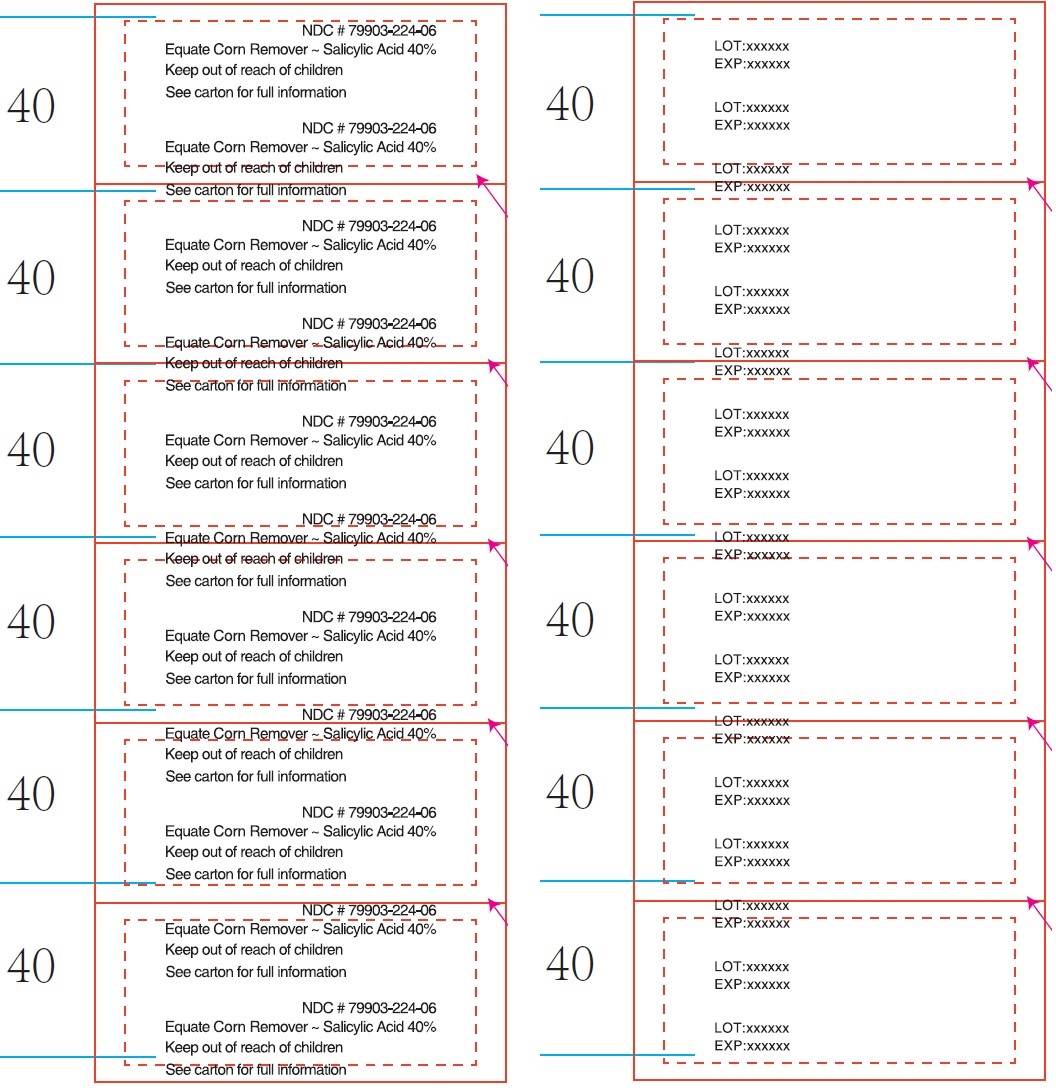 DRUG LABEL: Equate One-Step Medicated Corn Removers
NDC: 79903-224 | Form: PATCH
Manufacturer: Walmart Inc.
Category: otc | Type: HUMAN OTC DRUG LABEL
Date: 20250104

ACTIVE INGREDIENTS: SALICYLIC ACID 40 mg/100 mg
INACTIVE INGREDIENTS: PARAFFIN; PETROLATUM; LANOLIN

Equate One-Step Medicated Corn Removers

Active ingredient

Salicylic acid 40%

Purpose

Corn Remover

Use

- for the removal of corns.
- relieves pain by removing corns

Warnings

For external use only.

Ask a doctor before use if you have

- diabetes
- poor blood circulation

Stop use and ask a doctor if

discomfort persists

Keep out of reach of children.

If swallowed, get medical help or contact a Poison Control Center right away.

Directions

- wash affected area: may soak corn in warm water for 5 minutes
- dry area thoroughly
- remove bandage strips by peeling backing off
- adhere medicated patch directly over corn
- repeat this procedure every 48 hours as needed (until corn is removed) for up to 14 days

Other information

store between 59° and 86°F (15° and 30°C)

Inactive ingredients

lanolin, paraffin, petrolatum

Questions or comments?

1-888-287-1915